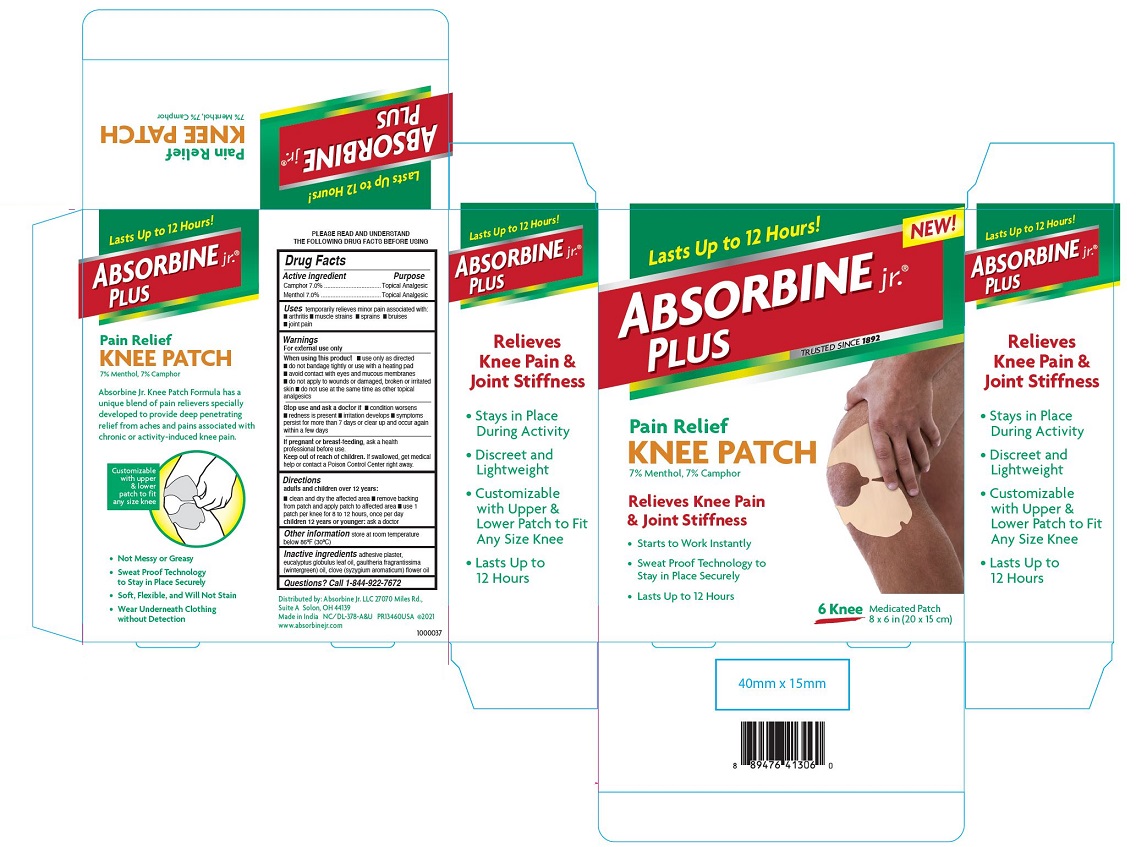 DRUG LABEL: ABSORBINE jr. PLUS Knee
NDC: 69693-416 | Form: PATCH
Manufacturer: Clarion Brands, LLC
Category: otc | Type: HUMAN OTC DRUG LABEL
Date: 20251223

ACTIVE INGREDIENTS: MENTHOL, UNSPECIFIED FORM 7 mg/100 mg; CAMPHOR (SYNTHETIC) 7 mg/100 mg
INACTIVE INGREDIENTS: EUCALYPTUS GLOBULUS LEAF; METHYL SALICYLATE; CLOVE OIL

Drug Facts

ACTIVE INGREDIENT

Active Ingredient | Purpose
Camphor 7.0% | Topical Analgesic
Menthol 7.0% | Topical Analgesic

INDICATIONS AND USAGE

Usestemporarily relieves minor pain associated with:

- arthritis
- muscle strains
- sprains
- bruises
- joint pain

Warnings

For external use only

When using this product

- use only as directed
- do not bandage tightly or use with a heating pad
- avoid contact with eyes and mucous membranes
- do not apply to wounds or damaged, broken or irritated skin
- do not use at the same time as other topical analgesics

Stop use and ask a doctor if

- condition worsens
- redness is present
- irritation develops
- symptoms persist for more that 7 days or clear up and occur again within a few days

PREGNANCY OR BREAST FEEDING

If pregnant or breast-feeding, ask a health professional before use.

Keep out of reach of children.If swallowed, get medical help or contact a Poison Control Center right away.

Directions
adults and children over 12 years:

- clean and dry the affected area
- remove backing from patch and apply patch to affected area
- use 1 patch for 8 to 12 hours, once a day

children 12 years or younger:ask a doctor

STORAGE AND HANDLING

Other informationstore at room temperature below 86ºF (30ºC)

INACTIVE INGREDIENT

Inactive ingredientsadhesive plaster, eucalyptus globulus leaf oil, gaultheria fragrantissima (wintergreen) oil, clove (syzygum aromaticum) flower oil

PRINCIPAL DISPLAY PANEL

Lasts Up to 12 Hours!
NEW!
Absorbine jr.®Plus
TRUSTED SINCE 1892
Pain Relief
KNEE PATCH
7% Menthol, 7% Camphor
Relieves Knee Pain
& Joint Stiffness
• Starts to Work Instantly
• Sweat Proof Technology to Stay in Place Securely
• Lasts up to 12 Hours
6 Knee
Medicated Patch
8 × 6 in (20 × 15 cm)
Absorbine Jr. Knee Patch Formula has a unique blend of pain relievers specially developed to provide deep penetrating relief from aches and pains associated with chronic or activity-induced knee pain.
Customizable with upper & lower patch to fit any size knee
• Not Messy or Greasy
• Sweat Proof Technology to Stay in Place Securely
• Soft, Flexible, and Will Not Stain
• Wear Underneath Clothing without Detection
Relieves Knee Pain & Joint Stiffness
• Stays in Place During Activity
• Discreet and Lightweight
• Customizable with Upper & Lower Patch to Fit Any Size Knee
• Lasts up to 12 Hours
Distributed by: Absorbine jr. LLC 27070 Miles Rd.,
Suite A Solon, OH 44139
Made in India NC/DL-378-A&U PR13460USA ©2021
www.absorbinejr.com
1000037